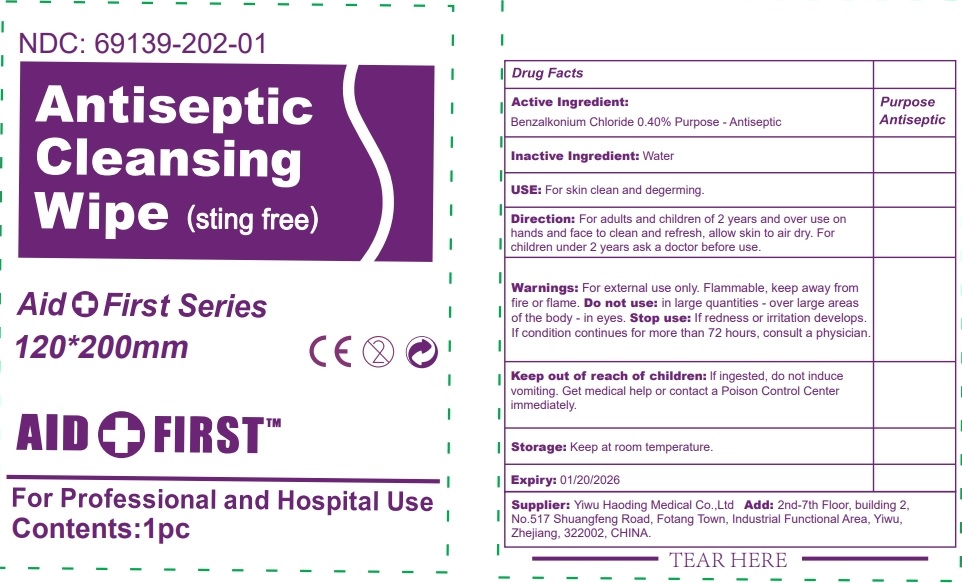 DRUG LABEL: aid and first antiseptic cleansing wipe
NDC: 69139-202 | Form: SWAB
Manufacturer: YIWU HAODING MEDICAL CO.,LTD
Category: otc | Type: HUMAN OTC DRUG LABEL
Date: 20240109

ACTIVE INGREDIENTS: BENZALKONIUM CHLORIDE 0.40 g/100 g
INACTIVE INGREDIENTS: WATER

Active Ingredients

Benzalkonium Chloride 0.40%

Purpose

Antiseptic

Use

skin clean and degerming

Warnings

for external use only.

flammable, keep away fro fire or flame

KEEP OUT OF REACH OF CHILDREN

if swallowed, get medical help or contact Poison control Center right away.

do not use

- in large quantities
- over large areas of the body
- in eyes

stop use and ask a doctor if conditions worsen or persist

Directions

for adults and childre of 2 years and over use on hands and face to clean and refresh, allow skin to air dry.

for childre under 2 years ask a doctor before use.

other information:

not intended for use of delicate or sensitive skin.

Inactive Ingredient

water